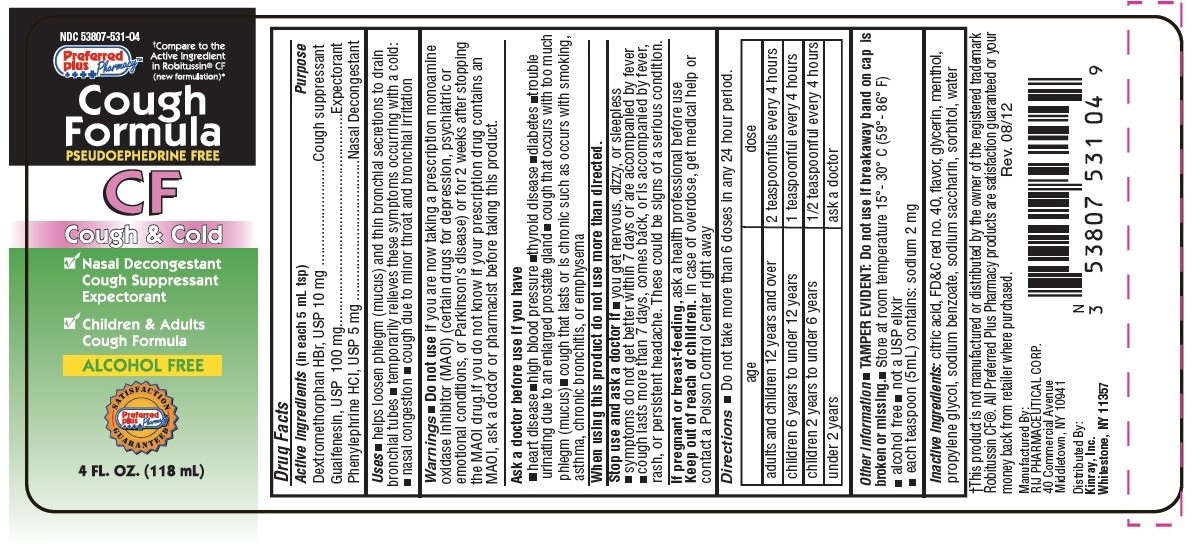 DRUG LABEL: Cough Formula Cough and Cold
NDC: 53807-531 | Form: LIQUID
Manufacturer: Rij Pharmaceutical Corporation
Category: otc | Type: HUMAN OTC DRUG LABEL
Date: 20180430

ACTIVE INGREDIENTS: DEXTROMETHORPHAN HYDROBROMIDE 10 mg/5 mL; GUAIFENESIN 100 mg/5 mL; PHENYLEPHRINE HYDROCHLORIDE 5 mg/5 mL
INACTIVE INGREDIENTS: ANHYDROUS CITRIC ACID; FD&C RED NO. 40; MENTHOL; SACCHARIN SODIUM; SODIUM BENZOATE; WATER; GLYCERIN

Drug Facts

Active ingredient (in each 5 mLtsp)

Dextromethorphan HBr, USP 10 mg

Guaifenesin, USP 100 mg

Phenylephrine HCl, USP 5 mg

Purpose

Cough suppressant

Expectorant

Nasal decongestant

Uses

helps loosen phlegm (mucus) and thin bronchial secretions to to drain bronchial tubes

temporarily relieves these symptoms occuring with a cold

nasal congestion

cough due to minor throat and bronchial irritation

Warnings

Do not use

- if you are now taking a prescription monoamine oxidase inhibitor (MAOI) (certain drugs for depression, psychiatric, or emotional conditions, or Parkinson's disease), or for 2 weeks after stopping the MAOI drug. If you do not know if your prescription drug contains an MAOI, ask a doctor or pharmacist before taking this product.

Ask a doctor before use if you have

- heart disease
- high blood pressure
- thyroid disease
- diabetes
- trouble urinating due to an enlarged prostate gland
- cough that occurs with too much phlegm (mucus)
- cough that lasts or is chronic such as occurs with smoking, asthma, chronic bronchitis, or emphysema

When using this product do not use more than directed.

Stop use and ask a doctor if

- you get nervous, dizzy, or sleepless
- symptoms do not get better within 7 days or are accompanied by fever
- cough that lasts more than 7 days, comes back, or is accompanied by fever, rash, or persistent headache. These could be signs of a serious condition.

PREGNANCY OR BREAST FEEDING

If pregnant or breast-feeding, ask a health professional before use.

Keep out of reach of children. In case of overdose, get medical help or contact a Poison Control Center right away.

Directions

- do not take more than 6 doses in any 24-hour period

age | dose
adults and children 12 years and over | 2 teaspoonfuls every 4 hours
children 6 years to under 12 years | 1 teaspoonful every 4 hours
children 2 years to under 6 years | 1/2 teaspoonful every 4 hours
children under 2 years | ask a doctor

Other information

- TAMPER EVIDENT: DO NOT USE IF BREAKAWAY BAND ON CAP IS BROKEN OR MISSING
- store at room temperature 15º - 30ºC (59º - 86ºF)
- alocohol free
- not a USP elixir
- each teaspoon (5 mL) contains: sodium 2 mg.

Inactive ingredients

citric acid, FD&C red no. 40, , flavors, glycerin, menthol, propylene glycol, sodium benzoate, sodium saccharin, water